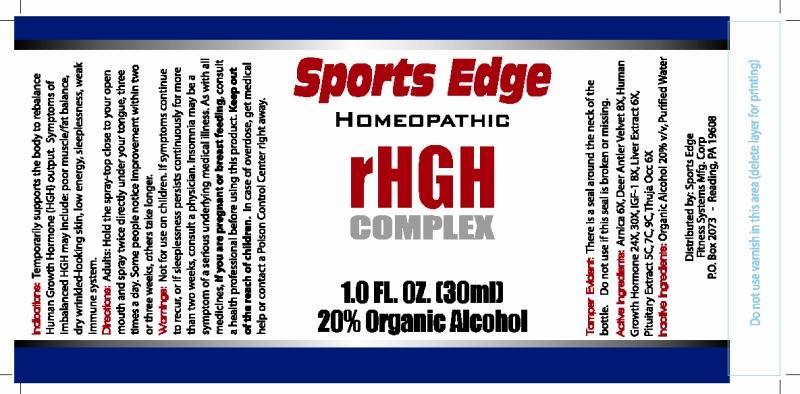 DRUG LABEL: rHGH Complex
NDC: 51609-0001 | Form: LIQUID
Manufacturer: Fitness Systems Mfg Corp
Category: homeopathic | Type: HUMAN OTC DRUG LABEL
Date: 20120927

ACTIVE INGREDIENTS: ARNICA MONTANA 6 [hp_X]/1 mL; CERVUS ELAPHUS VELVET 8 [hp_X]/1 mL; BEEF LIVER 6 [hp_X]/1 mL; SOMATROPIN 24 [hp_X]/1 mL; MECASERMIN 6 [hp_X]/1 mL; BOS TAURUS PITUITARY GLAND 5 [hp_C]/1 mL; THUJA OCCIDENTALIS LEAFY TWIG 6 [hp_X]/1 mL
INACTIVE INGREDIENTS: WATER; ALCOHOL

Drug Facts

ACTIVE INGREDIENTS

Arnica Montana 6X, Deer Antler Velvet 8X, Hepar Bovinum 6X, HGH 24X, 30X, IGF 1 8X, Pituitary Bovinum 5C, 7C, 9C, Thuja Occidentalis 6X.

INDICATIONS

Temporarily supports the body to rebalance Human Growth Hormone (HGH) output. Symptoms of Imbalanced HGH may Include: poor muscle/fat balance, dry wrinkled-looking skin, low energy, sleeplessness, weak immune system.

WARNINGS

Not for use on children. If symptoms continue to recur, or if sleeplessness persists continuously for more than two weeks, consult a physician. Insomnia may be a symptom of serious underlying medical illness. As with all medicines, if you are pregnant or breast feeding, consult a health professional before using this product. Keep out of reach of children. In case of overdose, get medical help or contact a Poison Control Center right away.

DIRECTIONS

Adults: Hold the spray top close to your open mouth and spray twice directly under your tongue, three times a day. Some people notice improvement within two or three weeks, others take longer.

INACTIVE INGREDIENTS

Organic Alcohol 20% v/v, Purified Water.

KEEP OUT OF REACH OF CHILDREN

In case of overdose, get medical help or contact a Poison Control Center right away.

INDICATIONS AND USAGE

Temporarily supports the body to rebalance Human Growth Hormone (HGH) output. Symptoms of Imbalanced HGH may Include: poor muscle/fat balance, dry wrinkled-looking skin, low energy, sleeplessness, weak immune system.

QUESTIONS

Distributed by: Sports Edge

Fitness Systems Mfg. Corp

P.O. Box 2073 Reading, PA 19608

PACKAGE LABEL

Sports Edge

HOMEOPATHIC

rHGH

COMPLEX

1.0 FL OZ (30ml)